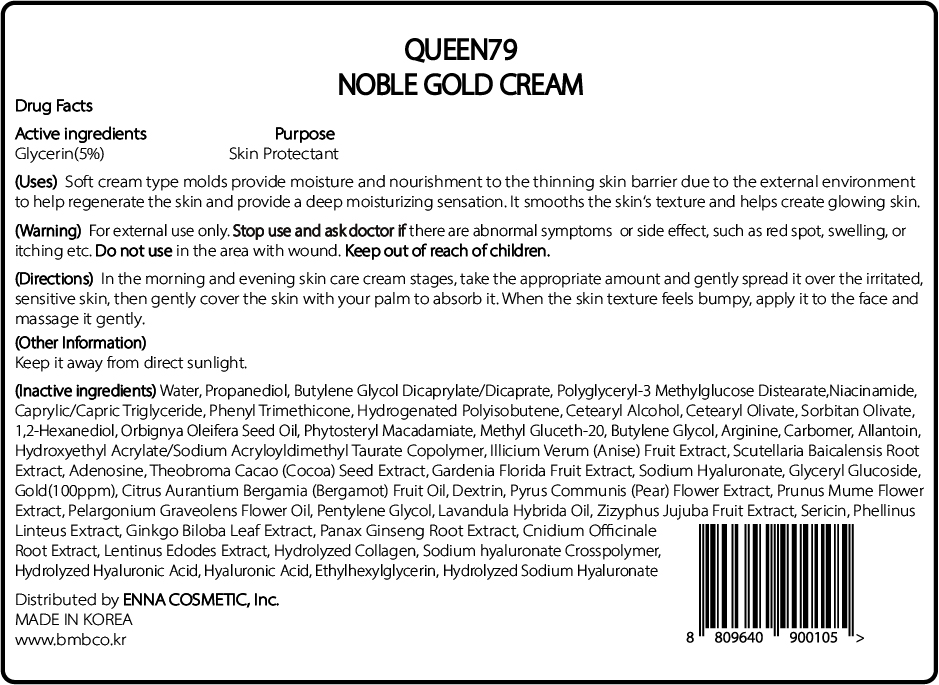 DRUG LABEL: QUEEN79 NOBLE GOLDCREAM
NDC: 81810-305 | Form: CREAM
Manufacturer: ENNA COSMETIC, Inc.
Category: otc | Type: HUMAN OTC DRUG LABEL
Date: 20230531

ACTIVE INGREDIENTS: GLYCERIN 5 mg/100 mL
INACTIVE INGREDIENTS: PRUNUS MUME FLOWER; BERGAMOT OIL; LENTINULA EDODES MYCELIUM; ASIAN GINSENG; CNIDIUM OFFICINALE ROOT; HYALURONATE SODIUM; HYALURONIC ACID; WATER; BUTYLENE GLYCOL DICAPRYLATE/DICAPRATE; MEDIUM-CHAIN TRIGLYCERIDES; HYDROGENATED POLYBUTENE (1300 MW); SORBITAN OLIVATE; 1,2-HEXANEDIOL; BUTYLENE GLYCOL; ALLANTOIN; HYDROXYETHYL ACRYLATE/SODIUM ACRYLOYLDIMETHYL TAURATE COPOLYMER (45000 MPA.S AT 1%); GINKGO; PROPANEDIOL; JUJUBE FRUIT; ETHYLHEXYLGLYCERIN; GARDENIA JASMINOIDES FRUIT; CETEARYL OLIVATE; STAR ANISE FRUIT; SCUTELLARIA BAICALENSIS ROOT; ARGININE; PELARGONIUM GRAVEOLENS FLOWER OIL; LAVANDIN OIL; SILK SERICIN; PENTYLENE GLYCOL; METHYL GLUCETH-20; ADENOSINE; ICODEXTRIN; COCOA; POLYGLYCERYL-3 METHYLGLUCOSE DISTEARATE; CETOSTEARYL ALCOHOL; CARBOMER HOMOPOLYMER, UNSPECIFIED TYPE; NIACINAMIDE; PYRUS COMMUNIS FLOWER; GOLD; PHENYL TRIMETHICONE; BABASSU OIL; PHYTOSTERYL MACADAMIATE

81810-305 QUEEN79 NOBLE GOLD CREAM

Active ingredients

Glycerin(5%)

Purpose

Skin Protectant

Uses

Soft cream type molds provides moistue and nourishment to the thinning skin barrier due to the external environment to help regenerate the skin and provide a deep moisturizing sensation. It smooths the skin's texture and helps create glowing skin.

Warning

For external use only

Stop use and ask doctor if

there are abnormal symptoms or side effects, such as red spot, swelling, or itching etc.

Do not use

in the area with wound.

Keep out of reach of children

Directions

In the morning and evening skin care cream stages, take the appropriate amount and gently spread it over the irritated, sensitive skin, then gently cover the skin with your palm to absorb it. When the skin texture feels bumpy, apply it to the face and massage it gently.

Other Information

Keep it away from direct sunlight.

Inactive ingredients

Water, Propanediol, Butylene Glycol Dicaprylate/Dicaprate, Polyglyceryl-3 Methylglucose Distearate, Niacinamide, Caprylic/Capric Triglyceride, Phenyl Trimethicone, Hydrogenated Polyisobutene, Cetearyl Alcohol, Cetearyl Olivate, Methyl Gluceth-20, Orbignya Oleifera Seed Oil, Phytosteryl Macadamiate, Arginine, Carbomer, Glyceryl Glucoside, Allantoin, Hydroxyethyl Acrylate/Sodium Acryloyldimethyl Taurate Copolymer, Gold(100ppm), Adenosine, Gardenia Florida Fruit Extract, Theobroma Cacao (Cocoa) Seed Extract, Zizyphus Jujuba Fruit Extract, Prunus Mume Flower Extract, Dextrin, Butylene Glycol, Pyrus Communis (Pear) Flower Extract, Sericin, Sodium Hyaluronate, Sodium hyaluronate Crosspolymer, Sorbitan Olivate, Ethylhexylglycerin, Ginkgo Biloba Leaf Extract, Panax Ginseng Root Extract, Phellinus Linteus Extract, Cnidium Officinale Root Extract, Pentylene Glycol, Lentinus Edodes Extract, Hydrolyzed Sodium Hyaluronate, Hydrolyzed Collagen, Hydrolyzed Hyaluronic Acid, Hyaluronic Acid, Citrus Aurantium Bergamia (Bergamot) Fruit Oil, Pelargonium Graveolens Flower Oil, Lavandula Hybrida Oil, Illicium Verum (Anise) Fruit Extract, Scutellaria Baicalensis Root Extract, 1,2-Hexanediol